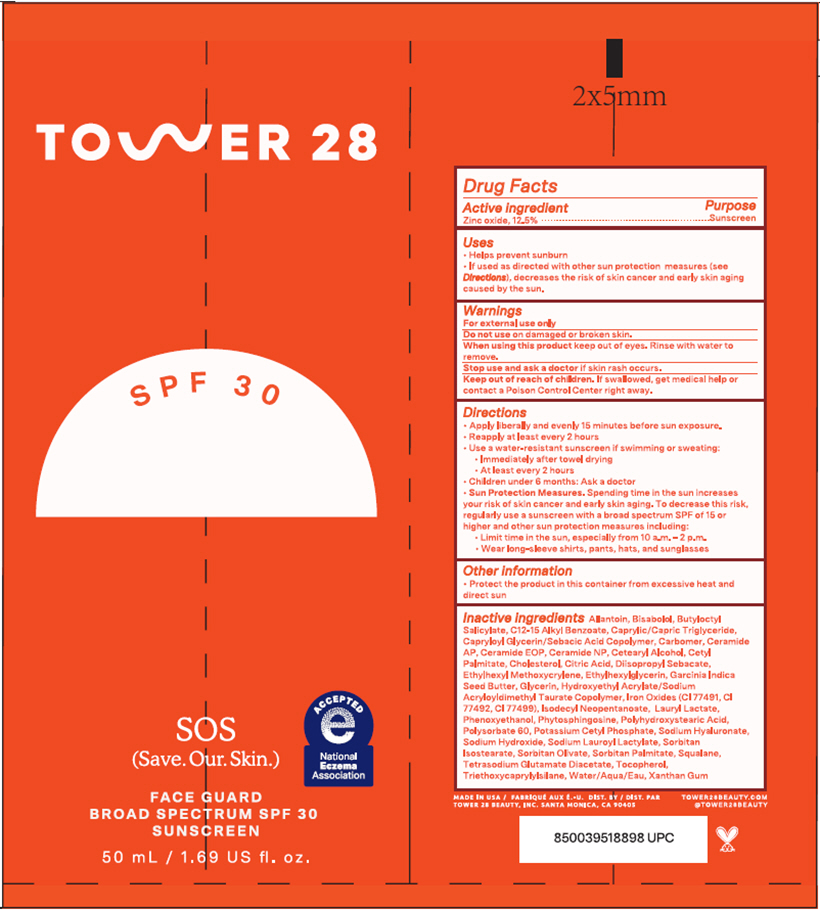 DRUG LABEL: SOS Face Guard Broad Spectrum Sunscreen SPF 30
NDC: 81899-152 | Form: LOTION
Manufacturer: Tower 28
Category: otc | Type: HUMAN OTC DRUG LABEL
Date: 20250128

ACTIVE INGREDIENTS: Zinc Oxide 125 mg/1 mL
INACTIVE INGREDIENTS: ALLANTOIN; .ALPHA.-BISABOLOL, (+)-; BUTYLOCTYL SALICYLATE; ALKYL (C12-15) BENZOATE; MEDIUM-CHAIN TRIGLYCERIDES; CAPRYLOYL GLYCERIN/SEBACIC ACID COPOLYMER (2000 MPA.S); CARBOMER HOMOPOLYMER, UNSPECIFIED TYPE; CERAMIDE AP; CERAMIDE 9; CERAMIDE NP; CETOSTEARYL ALCOHOL; CETYL PALMITATE; CHOLESTEROL; ANHYDROUS CITRIC ACID; DIISOPROPYL SEBACATE; ETHYLHEXYL METHOXYCRYLENE; ETHYLHEXYLGLYCERIN; GARCINIA INDICA SEED BUTTER; GLYCERIN; HYDROXYETHYL ACRYLATE/SODIUM ACRYLOYLDIMETHYL TAURATE COPOLYMER (100000 MPA.S AT 1.5%); ISODECYL NEOPENTANOATE; LAURYL LACTATE; PHENOXYETHANOL; PHYTOSPHINGOSINE; POLYHYDROXYSTEARIC ACID (2300 MW); POLYSORBATE 60; POTASSIUM CETYL PHOSPHATE; HYALURONATE SODIUM; SODIUM HYDROXIDE; SODIUM LAUROYL LACTYLATE; SORBITAN ISOSTEARATE; SORBITAN OLIVATE; SORBITAN MONOPALMITATE; SQUALANE; TETRASODIUM GLUTAMATE DIACETATE; TOCOPHEROL; TRIETHOXYCAPRYLYLSILANE; WATER; XANTHAN GUM; FERRIC OXIDE RED; FERRIC OXIDE YELLOW; FERROSOFERRIC OXIDE

SOS Face Guard Broad Spectrum Sunscreen SPF 30

Drug Facts

Active ingredient

Zinc oxide, 12.5%

Purpose

Sunscreen

Uses

- Helps prevent sunburn
- If used as directed with other sun protection measures (see Directions), decreases the risk of skin cancer and early skin aging caused by the sun.

Warnings

For external use only

Do not use on damaged or broken skin.

When using this product keep out of eyes. Rinse with water to remove.

Stop use and ask a doctor if skin rash occurs.

Keep out of reach of children. If swallowed, get medical help or contact a Poison Control Center right away.

Directions

- Apply liberally and evenly 15 minutes before sun exposure.
- Reapply at least every 2 hours
- Use a water-resistant sunscreen if swimming or sweating:
  - Immediately after towel drying
  - At least every 2 hours
- Children under 6 months: Ask a doctor
- Sun Protection Measures. Spending time in the sun increases your risk of skin cancer and early skin aging. To decrease this risk, regularly use a sunscreen with a broad spectrum SPF of 15 or higher and other sun protection measures including:
  - Limit time in the sun, especially from 10 a.m. - 2 p.m.
  - Wear long-sleeve shirts, pants, hats, and sunglasses

Other information

- Protect the product in this container from excessive heat and direct sun

Inactive ingredients

Allantoin, Bisabolol, Butyloctyl Salicylate, C12-15 Alkyl Benzoate, Caprylic/Capric Triglyceride, Capryloyl Glycerin/Sebacic Acid Copolymer, Carbomer, Ceramide AP, Ceramide EOP, Ceramide NP, Cetearyl Alcohol, Cetyl Palmitate, Cholesterol, Citric Acid, Diisopropyl Sebacate, Ethylhexyl Methoxycrylene, Ethylhexylglycerin, Garcinia Indica Seed Butter, Glycerin, Hydroxyethyl Acrylate/Sodium Acryloyldimethyl Taurate Copolymer, Iron Oxides (CI 77491, CI 77492, CI 77499), Isodecyl Neopentanoate, Lauryl Lactate, Phenoxyethanol, Phytosphingosine, Polyhydroxystearic Acid, Polysorbate 60, Potassium Cetyl Phosphate, Sodium Hyaluronate, Sodium Hydroxide, Sodium Lauroyl Lactylate, Sorbitan Isostearate, Sorbitan Olivate, Sorbitan Palmitate, Squalane, Tetrasodium Glutamate Diacetate, Tocopherol, Triethoxycaprylylsilane, Water/Aqua/Eau, Xanthan Gum

DIST. BY
TOWER 28 BEAUTY, INC. SANTA MONICA, CA 90405

PRINCIPAL DISPLAY PANEL - 50 mL Tube Box Label

TOWER 28

SPF 30

SOS
(Save. Our. Skin.)

ACCEPTED
e
National
Eczema
Association

FACE GUARD
BROAD SPECTRUM SPF 30
SUNSCREEN

50 mL / 1.69 US fl. oz.